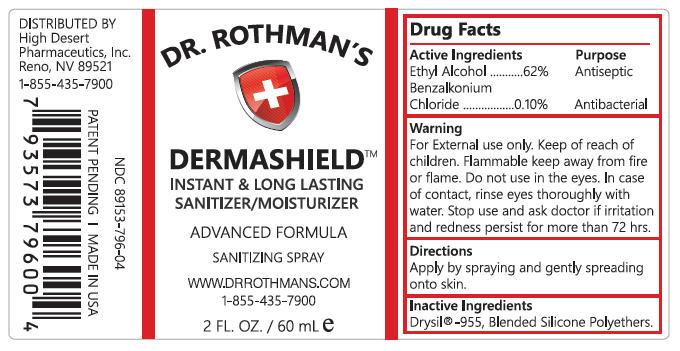 DRUG LABEL: Dr. Rothmans Dermashield
NDC: 89153-796 | Form: SPRAY
Manufacturer: High Desert Pharmaceutics, Inc.
Category: otc | Type: HUMAN OTC DRUG LABEL
Date: 20141204

ACTIVE INGREDIENTS: Alcohol 37.2 g/60 g; Benzalkonium Chloride 0.06 g/60 g
INACTIVE INGREDIENTS: Dimethicone

Dr. Rothman's Dermashield Instant & Long Lasting Sanitizer/Moisturizer Advanced Formula Sanitizing Spray

Active Ingredients

- Ethyl Alcohol - 62%
- Benzalkonium Chloride - 0.10%

Warning

- Keep out of reach of children.

Purpose

- Antiseptic
- Antibacterial

Directions

- Apply by spraying and gently spreading onto skin.

Warning

- For external use only.
- Flammable keep away from fire or flame
- Do not use in eyes. In case of contact, rinse eyes thoroughly with water.

Warning

- Stop use and ask doctor if irritation and redness persist for more than 72 hours.

INDICATIONS AND USAGE

Sanitizer and moisturizer

DOSAGE AND ADMINISTRATION

Apply by spraying and gently spreading onto skin

INACTIVE INGREDIENT

Blended Silicone Polyethers

PACKAGE LABEL

Dr Rothman's Dermashield